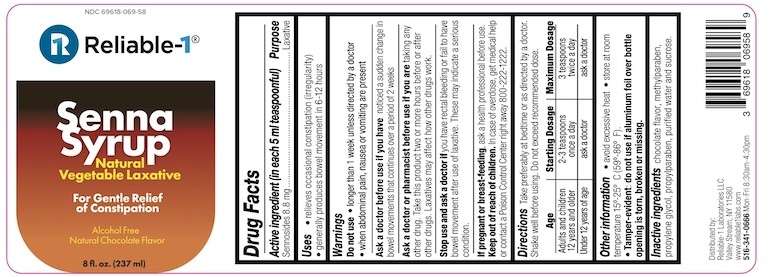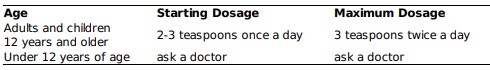 DRUG LABEL: SENNA
NDC: 69618-069 | Form: SYRUP
Manufacturer: Reliable 1 Laboratories LLC
Category: otc | Type: HUMAN OTC DRUG LABEL
Date: 20250211

ACTIVE INGREDIENTS: SENNOSIDES 8.8 mg/5 mL
INACTIVE INGREDIENTS: PROPYLPARABEN; METHYLPARABEN; WATER; PROPYLENE GLYCOL; SUCROSE

Senna Syrup

ACTIVE INGREDIENT (IN EACH 5mL TEASPOONFUL)

Sennosides 8.8 mg

PURPOSE

Laxative

USES

- relieves occasional constipation (irregularity)
- generally produces bowel movement is 6-12 hours

Do Not Use

- longer than 1 week unless directed by a doctor
- when abdominal pain, nausea or vomiting are present

Ask a doctor before use if you have noticed a sudden change in bowel movements that continues over a period of 2 weeks

Ask a doctor or pharmacist before use if you are taking any other drug. Take this product two or more hours before or after other drgus. Laxatives may affect how other drugs work.

Stop use and ask a doctor if you have rectal bleeding or fail to have a bowel movement after use of a laxative. These may indicate a serious condition.

If pregnant or breast-feeding, ask a health professional before use.

Keep out of reach of children. In case of overdose, get medical help or contact a Poison Control Center right away 800-222-1222.

Directions

Take preferably at bedtime or as directed by a doctor. Shake well before using. Do not exceed recommended dose.

Other Information

- avoid excessive heat
- store at room temperature 15°-25°C (59°-86°F).
- Tamper-evident: do not use if aluminum foil seal over bottle opening is torn, broken or missing.

Inactive ingredients

chocolate flavor, methylparaben, propylene glycol, propylparaben, purified water and sucrose.

PACKAGE LABEL

NDC 69618-069-58

Reliable-1®

Senna Syrup

Natural Vegetable Laxative

For Gentle Relief of Constipation

Alcohol Free

Natural Chocolate Flavor

8 fl. oz. (237 ml)

Distributed by: Reliable-1 Laboratories LLC Valley Stream, NY 11580

www.reliable1labs.com

516-341-0666 Mon-Fri 8:30am-4:30pm